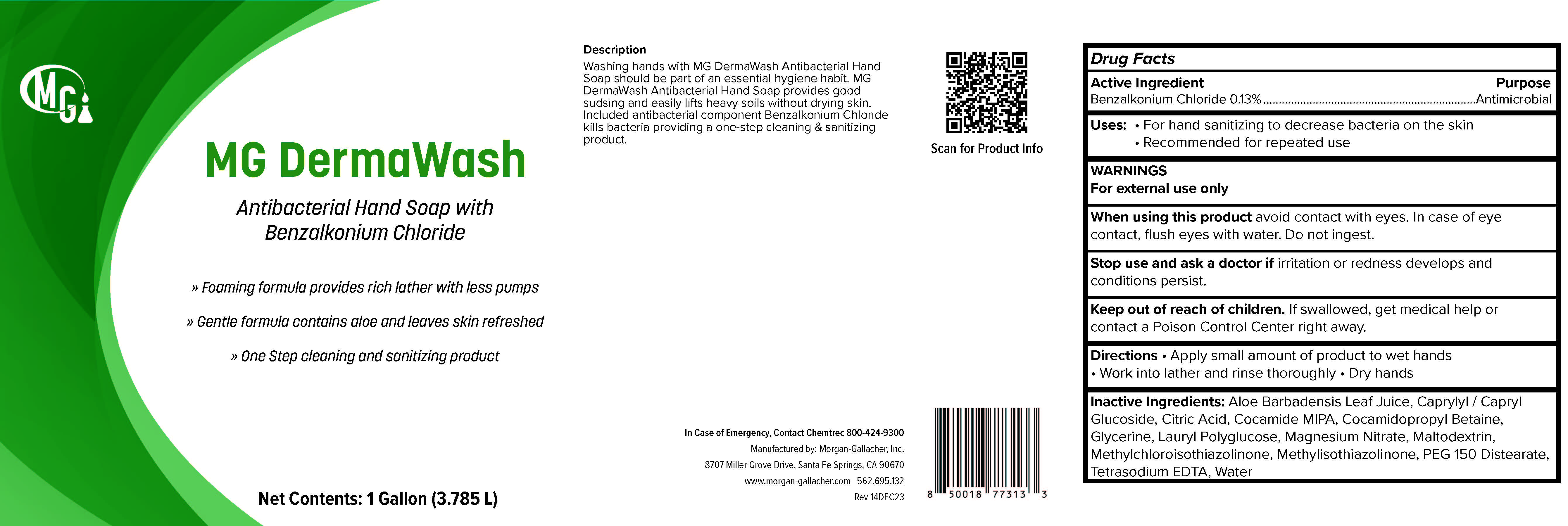 DRUG LABEL: MG DermaWash
NDC: 50241-302 | Form: LIQUID
Manufacturer: Morgan Gallacher Inc. DBA Custom Chemical Formulators Inc.
Category: otc | Type: HUMAN OTC DRUG LABEL
Date: 20251223

ACTIVE INGREDIENTS: BENZALKONIUM CHLORIDE 13 kg/100 kg
INACTIVE INGREDIENTS: ALOE VERA FLOWER; CAPRYLYL/CAPRYL OLIGOGLUCOSIDE; ANHYDROUS CITRIC ACID; COCO MONOISOPROPANOLAMIDE; COCAMIDOPROPYL BETAINE; GLYCERIN; LAURYL GLUCOSIDE; MAGNESIUM NITRATE; MALTODEXTRIN; METHYLCHLOROISOTHIAZOLINONE; METHYLISOTHIAZOLINONE; PEG-150 DISTEARATE; EDETATE SODIUM; WATER

MG DermaWash

ACTIVE INGREDIENT

Benzalkonium Chloride......0.13%

Purpose

Antiseptic

Uses

For hand sanitizing to decrease bacteria on the skin.

Recommended for repeated use.

Warnings

For external use only.

When Using this Product

- Avoid contact with eyes. In case of eye contact,, flush eyes with water.

- Do not ingest. Stop use and contact a doctor if irritation or

redness develop or conditions persist.

Keep out of reach of children.

If swallowed, get medical help

or contact Poison Control Center right away.

Directions

- Apply small amount of product to wet hands.

- Work into lather and rinse thogoughly. Dry hands.

INERT INGREDIENTS:

Aloe Barbadensis Leaf Juice, Caprylyl/Capryl Gluciside, Citric Acid, Cocamide MIPA, Cocamidopropyl Betaine, Glycerin, Lauryl Polyglucose, Magnesium Nitrate, Maltodextrin, Methylchloroisothiazolinone, Methylthiazolinone, PEG
150 Distearate, Tetrasodium EDTA, Water